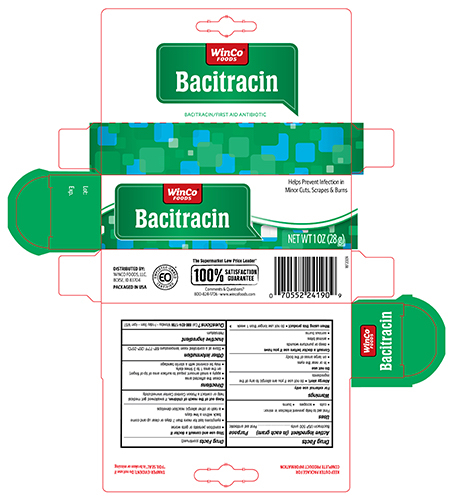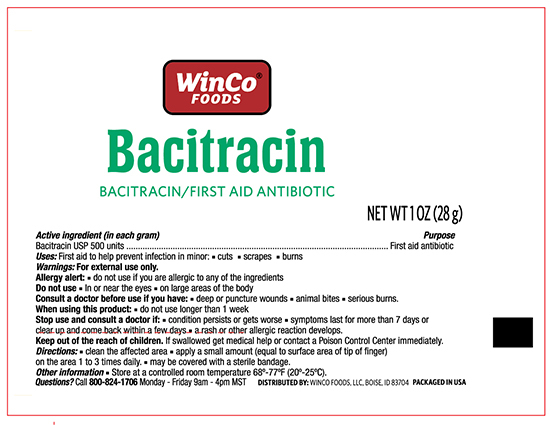 DRUG LABEL: Winco Bacitracin Zinc
NDC: 67091-270 | Form: OINTMENT
Manufacturer: WinCo Foods, LLC
Category: otc | Type: HUMAN OTC DRUG LABEL
Date: 20241121

ACTIVE INGREDIENTS: BACITRACIN ZINC 500 [USP'U]/1 g
INACTIVE INGREDIENTS: PETROLATUM

Winco Bacitracin Zinc Ointment 1OZ

Active ingredient (in each gram) Purpose

Bacitracin 500 units...............................................................................First aid antibiotic

PURPOSE

Uses first aid to help prevent infection in minor:

- cuts
- scrapes
- burns

Warnings

For external use only

Do not use

- in the eyes
- over large areas of the body
- if you are allergic to any of the ingredients

Ask a doctor if you have

- deep or puncture wounds
- animal bites
- serious burns

Stop use and ask a doctor if

- you need to use longer than 1 week
- the condition persists or gets worse
- rash or other allergic reaction develops

Keep out of reach of children. If swallowed, get medical help or contact a Poison Control Center right away.

Directions

- clean the affected area
- apply a small amount of this product (an amount equal to the surface area of the tip of a finger) on the area 1 to 3 times daily
- may be covered with a sterile bandage

Other information

- store between 20° to 25°C (68° to 77°F)
- Lot No. & Exp. Date: see box or see crimp of tube

Inactive ingredients

Petrolatum

QUESTIONS

Questions? Or to report an adverse event call 800-824-1706 Monday - Friday 9am - 4pm MST

DOSAGE AND ADMINISTRATION

DISTRIBUTED BY: WINCO FOODS, LLC BOISE, ID 83704

PACKAGE LABEL

Winco Bacitracin Zinc NDC 67091-270-28

1 OZ (28g)

PACKAGE LABEL

Winco Bacitracin NDC 67091-270-28

NET WT 1 OZ (28g)